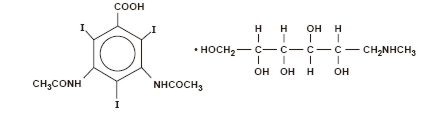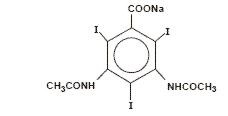 DRUG LABEL: Unknown
Manufacturer: Amersham Health Inc.
Category: prescription | Type: HUMAN PRESCRIPTION DRUG LABELING
Date: 20060413

HYPAQUE™-76
(Diatrizoate Meglumine and Diatrizoate Sodium Injection, USP)
76%

Sterile Aqueous Injection

For Excretory Urography
Aortography
Angiocardiography (Ventriculography, Pulmonary
Angiography, Selective Coronary Arteriography)
Peripheral Angiography (Peripheral Arteriography
and Peripheral Venography)
Intravenous Digital Arteriography
Contrast Enhancement of Computed
Tomographic Head Imaging
Contrast Enhancement of Computed
Tomographic Body Imaging
Selective Renal Arteriography
Selective Visceral Arteriography
Central Venography
Renal Venography

NOT FOR INTRATHECAL USE

DESCRIPTION

HYPAQUE-76, brand of diatrizoate meglumine and diatrizoate sodium, is a water-soluble, radiopaque diagnostic medium. It is supplied as a 76 percent sterile aqueous solution providing 66 percent (w/v) diatrizoate meglumine and 10 percent (w/v) diatrizoate sodium. It is a triiodinated benzoic acid derivative containing 37 percent (w/v) organically bound iodine. Each mL contains 370 mg iodine and 3.68 mg (0.16 mEq) sodium. It is constituted as a radiopaque iodinated anion, diatrizoate, and the radiolucent cations meglumine and sodium. It is the organically bound iodine of the anion which opacifies internal structures for x-ray visualization and fluoroscopy.

The solution is hypertonic to blood with an osmolality of 2016 mosm/kg (determined by VPO). The viscosity is 9 cp at 37° C. The pH is adjusted between 6.0 and 7.7 using Na2CO3 with HCl or NaOH. The pKa is 3.4 for diatrizoic acid. Edetate calcium disodium 0.01 percent has been added as a sequestering stabilizing agent. The solution is clear, colorless to pale yellow.

Diatrizoate meglumine is 1-deoxy-1-(methylamino)-D-glucitol 3, 5-diacetamido-2,4,6-triiodobenzoate (salt) and has the following structural formula:

Diatrizoate sodium is monosodium, 3, 5-diacetamido-2,4,6-triiodobenzoate and has the following structural formula:

CLINICAL PHARMACOLOGY

Intravascular injection of a radiopaque diagnostic agent opacifies those vessels in the path of the flow of the contrast medium, permitting radiographic visualization of the internal structures of the human body until significant hemodilution occurs.

At physiologic pH, the water-soluble contrast media are completely dissociated into a radiopaque anion and a solubilizing cation. While circulating in tissue fluids, the compound remains ionized. However, it is not metabolized but excreted unchanged in the urine, each diatrizoate molecule remaining "obligated" to its sodium or meglumine moiety.

Following intravenous injection, the radiopaque diagnostic agents are immediately diluted in the circulating plasma. Equilibrium is reached with the extracellular compartment at about 10 minutes. Hence, the plasma concentration at 10 minutes is closely related to the dose corrected to body size.

The pharmacokinetics of the intravenously administered radiopaque contrast media are usually best described by a two compartment model with a rapid alpha phase for drug distribution and a slow beta phase for drug elimination. In patients with normal renal function, the alpha and beta half-lives were respectively 30 minutes and 120 minutes for diatrizoate. But in patients with renal functional impairment, the elimination half-life for the beta phase can be prolonged up to several days.

Injectable radiopaque diagnostic agents are excreted either through the liver or through the kidneys. These two excretory pathways are not mutually exclusive, but the main route of excretion seems to be governed by the affinity of the contrast medium for serum albumin. From 0% to 10% of diatrizoate sodium is bound to serum protein.

Diatrizoate salts are excreted unchanged predominantly through the kidneys by glomerular filtration. The amount excreted by the kidney during any period of time is determined by the filtered load; i.e., the product of plasma contrast media concentration and glomerular filtration rate. The plasma concentration is dependent upon the dose administered and the body size. The glomerular filtration rate varies with the body size, sex, age, circulatory dynamics, diuretic effect of the drug, and renal function. In patients with normal renal function the maximum urinary concentration of diatrizoate meglumine and diatrizoate sodium occurs within 10 minutes with 12 percent of the administered dose being excreted. The mean values of cumulative urinary excretion for diatrizoate meglumine and diatrizoate sodium expressed as percentage of administered dose are 38 percent at 60 minutes, 45 percent at 3 hours, and 94 to 100 percent at 24 hours.

Urinary excretion of contrast media is delayed in infants younger than 1 month and in patients with urinary tract obstruction. The urinary iodine concentration is higher with the sodium salt of diatrizoic acid than with the meglumine salt.

The liver and small intestine provide the major alternate route of excretion for diatrizoate. In patients free of severe renal disease, the fecal recovery is less than 2 percent of the administered dose. In patients with severe renal impairment the excretion of these contrast media through the gallbladder and into the small intestine sharply increases; up to 20 percent of the administered dose has been recovered in the feces in 48 hours.

Saliva is a minor secretory pathway for injectable radiopaque diagnostic agents. In patients with normal renal function, minimal amounts of contrast media are secreted unchanged. However, in uremic patients small amounts of free iodides resulting from deiodination prior to administration or in vivo, have been detected in the saliva.

Diatrizoate salts cross the placental barrier in humans by simple diffusion and appear to enter fetal tissue passively. No apparent harm to the fetus was observed when diatrizoate sodium and diatrizoate meglumine were injected intravenously 24 hours prior to delivery. However, abnormal neonatal opacification of the small intestine and colon were detected 4 to 6 days after delivery. Procedures including radiation involve a certain risk related to the exposure of the fetus. (See PRECAUTIONS—General, Pregnancy Category C.)

Injectable radiopaque diagnostic agents are excreted unchanged in human milk. (See PRECAUTIONS—General, Nursing Mothers.)

Computed Tomography

HYPAQUE-76 enhances computed tomographic brain scanning through augmentation of radiographic efficiency. The degree of enhancement of visualization of tissue density is directly related to the iodine content in an administered dose; peak iodine blood levels occur immediately following rapid injection of the dose. These levels fall rapidly within five to ten minutes. This can be accounted for by the dilution in the vascular and extracellular fluid compartments which causes an initial sharp fall in plasma concentration. Equilibration with the extracellular compartments is reached in about ten minutes; thereafter, the fall becomes exponential. Maximum contrast enhancement frequently occurs after peak blood iodine levels are reached. The delay in maximum contrast enhancement can range from five to forty minutes, depending on the peak iodine levels achieved and the cell type of the lesion. This lag suggests that radiographic contrast enhancement is at least in part dependent on the accumulation of iodine within the lesion and outside the blood pool, although the mechanism by which this occurs is not clear. The radiographic enhancement of nontumoral lesions, such as arteriovenous malformations and aneurysms, is probably dependent on the iodine content of the circulating blood pool.

In brain scanning, HYPAQUE-76, brand of diatrizoate meglumine and diatrizoate sodium injection, does not accumulate in normal brain tissue due to the presence of the blood-brain barrier. The increase in x-ray absorption in normal brain is due to the presence of contrast agent within the blood pool. A break in the blood-brain barrier such as occurs in malignant tumors of the brain allows the accumulation of the contrast medium within the interstitial tumor tissue. Adjacent normal brain tissue does not contain the contrast medium.

In nonneural tissues (during computed tomography of the body), diatrizoate diffuses rapidly from the vascular into the extravascular space. Increase in x-ray absorption is related to blood flow, concentration of the contrast medium, and extraction of the contrast medium by interstitial tumor tissue since no barrier exists. Contrast enhancement is thus due to the relative differences in extravascular diffusion between normal and abnormal tissue, quite different from that in the brain.

The pharmacokinetics of diatrizoate in both normal and abnormal tissue have been shown to be variable. Contrast enhancement appears to be greatest soon after administration of the contrast medium, and following intra-arterial rather than intravenous administration. The greatest enhancement can be detected by a series of consecutive two- to three-second scans performed just after injection (within 30 to 90 seconds), i.e., dynamic computed tomographic scanning.

Effects of Steroid Therapy

The anti-inflammatory and antiedema effects in patients receiving steroid therapy have interfered with the expected distribution of CT tissue enhancement on the scan in certain diseases.

INDICATIONS AND USAGE

HYPAQUE-76 is indicated for excretory urography, aortography, angiocardiography (ventriculography, pulmonary angiography, selective coronary arteriography), peripheral angiography (peripheral arteriography and peripheral venography), intravenous digital arteriography, contrast enhancement of computed tomographic head imaging, contrast enhancement of computed tomographic body imaging, selective renal arteriography, selective visceral arteriography, central venography, and renal venography.

In addition to the following generalCONTRAINDICATIONS, WARNINGS, PRECAUTIONS, and ADVERSE REACTIONS, there are additional listings in these categories under the particular procedures.

CONTRAINDICATIONS—General

HYPAQUE-76 has no absolute contraindications in its recommended uses (see general WARNINGS and PRECAUTIONS).

Do not use HYPAQUE-76 for myelography or for examination of dorsal cysts or sinuses which might communicate with the subarachnoid space. Even a small amount in the subarachnoid space may produce convulsions and result in fatality. (See also AORTOGRAPHY, Warnings.) Epidural injection is also contraindicated.

HYPAQUE-76 should not be injected directly into the carotid, vertebral, or spinal arteries.

HYPAQUE-76 is contraindicated in patients with a hypersensitivity to salts of diatrizoic acid.

Urography is contraindicated in patients with anuria.

Urography and large dose vascular procedures are contraindicated in dehydrated azotemic patients. (See also PRECAUTIONS—General.)

WARNINGS—General

SEVERE ADVERSE EVENTS - INADVERTENT INTRATHECAL ADMINISTRATION

Serious adverse reactions have been reported due to the inadvertent intrathecal administration of iodinated contrast media that are not indicated for intrathecal use. These serious adverse reactions include: death, convulsions, cerebral hemorrhage, coma, paralysis, arachnoiditis, acute renal failure, cardiac arrest, seizures, rhabdomyolysis, hyperthermia, and brain edema. Special attention must be given to insure that this drug product is not administered intrathecally.

Ionic iodinated contrast media inhibit blood coagulation, in vitro, more than nonionic contrast media. Nonetheless, it is prudent to avoid prolonged contact of blood with syringes containing ionic contrast media.

Serious, rarely fatal, thromboembolic events causing myocardial infarction and stroke have been reported during angiographic procedures with both ionic and nonionic contrast media. Therefore, meticulous intravascular administration technique is necessary, particularly during angiographic procedures, to minimize thromboembolic events. Numerous factors, including length of procedure, catheter and syringe material, underlying disease state and concomitant medications may contribute to the development of thromboembolic events. For these reasons, meticulous angiographic techniques are recommended including close attention to guidewire and catheter manipulation, use of manifold systems and/or three-way stopcocks, frequent catheter flushing with heparinized saline solutions and minimizing the length of the procedure. The use of plastic syringes in place of glass syringes has been reported to decrease but not eliminate the likelihood of in vitro clotting.

Excretory urography is potentially hazardous in patients with multiple myeloma. In some of those patients, therapeutically resistant anuria resulting in progressive uremia, renal failure, and eventually death has followed this procedure. Although neither the contrast agent nor dehydration has been proved separately to be the cause of anuria in myelomatous patients, it has been speculated that the combination of both may be causative. The risk of excretory urography in myelomatous patients is not a contraindication to the procedure; however, they require special precautions. Partial dehydration in the preparation of these patients for the examination is not recommended since this may predispose to the precipitation of myeloma protein in the renal tubules. Myeloma, which occurs most commonly in persons over age 40, should be considered before instituting urographic procedures.

Contrast media may promote sickling in individuals who are homozygous for sickle cell disease when the material is injected intravenously or intra-arterially.

Administration of radiopaque materials to patients known or suspected of having pheochromocytoma should be performed with extreme caution. If, in the opinion of the physician, the possible benefits of such procedures outweigh the considered risks, the procedures may be performed; however, the amount of radiopaque medium injected should be kept to an absolute minimum. The blood pressure should be assessed throughout the procedure and measures for treatment of a hypertensive crisis should be available.

Recent reports of thyroid storm occurring following the intravascular use of iodinated radiopaque diagnostic agents in patients with hyperthyroidism or with an autonomously functioning thyroid nodule suggest that this additional risk be evaluated in such patients before use of diatrizoate salts.

Contrast media administered for cardiac catheterization and angiocardiography may cause cellular injury to circulating lymphocytes. Chromosomal damage in humans includes inhibition of mitosis, increases in the number of micronuclei, and chromosome aberrations. The damages appear to be related to the contrast medium itself rather than to the x-ray radiation. It is to be noted that those agents have not been adequately tested in animal or laboratory systems.

Urography should be performed with caution in patients with severely impaired renal function and patients with combined renal and hepatic disease.

Subcutaneous extravasation causes transitory stinging, chiefly because of hypertonic cellulitis. If the volume extravasated is small, ill effects are very unlikely. However, if the extravasation is extensive, especially in poorly vascularized areas (e.g., dorsum of the foot or hand), and especially in the presence of vascular disease, skin slough may occur. Injection of sterile water to dilute or addition of spreading agents to speed absorption have not been successful and may aggravate the condition.

Selective spinal arteriography or arteriography of trunks providing spinal branches can cause mild to severe muscle spasm. However, serious neurologic sequelae, including permanent paralysis, could occur with even small doses of the 76 percent concentration.

In patients with subarachnoid hemorrhage, a rare association between contrast administration and clinical deterioration, including convulsions and death, has been reported. Therefore, administration of intravascular iodinated ionic contrast media in these patients should be undertaken with caution.

PRECAUTIONS—General

Diagnostic procedures which involve the use of radiopaque diagnostic agents should be carried out under the direction of personnel with the prerequisite training and with a thorough knowledge of the particular procedure to be performed. Appropriate facilities should be available for coping with any complication of the procedure, as well as for emergency treatment of severe reactions to the contrast agent itself. After parenteral administration of a radiopaque agent, competent personnel and emergency facilities should be available for at least 30 to 60 minutes since severe delayed reactions have occurred (see ADVERSE REACTIONS—General).

The possibility of a reaction, including serious, life-threatening, fatal, anaphylactic or cardiovascular reactions should always be considered (see ADVERSE REACTIONS). It is of utmost importance that a course of action be carefully planned in advance for immediate treatment of serious reactions, and that adequate and appropriate personnel be readily available in case of any reaction.

The possibility of an idiosyncratic reaction in susceptible patients should always be considered (see ADVERSE REACTIONS—General). The susceptible population includes patients with a history of a previous reaction to a contrast media, patients with a known sensitivity to iodine per se, and patients with a known clinical hypersensitivity: bronchial asthma, hay fever, and food allergies.

The occurrence of severe idiosyncratic reactions has prompted the use of several pretesting methods. However, pretesting cannot be relied upon to predict severe reactions and may itself be hazardous for the patient. It is suggested that a thorough medical history with emphasis on allergy and hypersensitivity, prior to the injection of any contrast media, may be more accurate than pretesting in predicting potential adverse reactions.

A positive history of allergies or hypersensitivity does not arbitrarily contraindicate the use of a contrast agent, where a diagnostic procedure is thought essential, but caution should be exercised (see ADVERSE REACTIONS—General). Premedication with antihistamines or corticosteroids to avoid or minimize possible allergic reactions in such patients should be considered. Recent reports indicate that such pretreatment does not prevent serious life-threatening reactions, but may reduce both their incidence and severity.

Preparatory dehydration for angiography and CT procedures is unnecessary and may be dangerous, contributing to acute renal failure in infants, young children, the elderly, patients with preexisting renal insufficiency, patients with advanced vascular disease, and diabetic patients. Dehydration in these patients seems to be enhanced by the osmotic diuretic action of urographic agents. Overnight fluid restriction for urography may be undesirable and is considered unnecessary when using this relatively high (76%) concentration.

Although azotemia is not a contraindication, the medium should be used with great care in patients with advanced renal destruction associated with severe uremia. (See also EXCRETORY UROGRAPHY, Precautions.)

Acute renal failure has been reported in diabetic patients with diabetic nephropathy and in susceptible nondiabetic patients (often elderly with preexisting renal disease) following excretory urography. Therefore, careful consideration of the potential risks should be given before performing this radiographic procedure in these patients. (See also EXCRETORY UROGRAPHY, Precautions—Preparatory Dehydration.)

Immediately following surgery, excretory urography should be used with caution in renal transplant recipients.

Due to the transitory increase in the circulatory osmotic load, injections of urographic agents should be used with caution in patients with congestive heart failure. Such patients should be observed for several hours following the procedure to detect delayed hemodynamic disturbances.

General anesthesia may be indicated in the performance of some procedures, in young or uncooperative children and in selected adult patients; however, a higher incidence of adverse reactions has been reported in these patients, and may be attributable to the inability of the patient to identify untoward symptoms, or to the hypotensive effect of anesthesia, which can reduce cardiac output and increase the duration of exposure to the contrast agent.

Seizure activity is rare (about 0.01%) on intravenous injection of ionic contrast media. However, in the higher doses used for CT in patients with brain metastases the incidence can be much higher (1% to 10%). In these patients prophylactic use of a small parenteral dose of diazepam is suggested immediately before injection when extra high dose CT regimens are employed.

In addition to the general precautions already described, excretory urography, angiography, and other uses also have hazards associated with the particular techniques employed. (See INDIVIDUAL INDICATIONS AND USAGE section.)

Information for Patients

Patients receiving injectable radiopaque diagnostic agents should be instructed to:

1. Inform the physician if they are pregnant (see CLINICAL PHARMACOLOGY).
2. Inform the physician if they are diabetic or if they have multiple myeloma, pheochromocytoma, homozygous sickle cell disease or known thyroid disorder (see WARNINGS—General).
3. Inform the physician if they are allergic to any drugs, food, or if they have had any reactions to previous injections of dyes used for x-ray procedures (see PRECAUTIONS—General).
4. Inform the physician about any other medications they are currently taking, including nonprescription drugs, before they are administered this drug.

Drug Interactions

Renal toxicity has been reported in a few patients with liver dysfunction who were given oral cholecystographic agents followed by urographic agents. Administration of intravascular urographic agents should therefore be postponed in any patient with a known or suspected hepatic or biliary disorder who has recently received a cholecystographic contrast agent.

Addition of an inotropic agent to contrast agents may produce a paradoxical depressant response which can be deleterious to the ischemic myocardium.

Diphenhydramine hydrochloride may cause precipitation when mixed in the same syringe with HYPAQUE-76.

Under certain circumstances (pH, temperature, concentrations, time), diatrizoate solutions are incompatible with promethazine hydrochloride, diphenhydramine hydrochloride, brompheniramine maleate, or papavarine hydrochloride solutions.

Do not prefill plastic syringes with HYPAQUE-76 for prolonged periods (i.e., for several hours or longer) before use.

Drug/Laboratory Test Interactions

If any of these studies, which might be affected by contrast media, are indicated, it is recommended that they be performed prior to administration of the contrast medium or two or more days afterwards.

Diatrizoate salts interfere with several laboratory urine and blood tests.

Blood Tests

Coagulation: Diatrizoate salts significantly inhibit all stages of coagulation. The fibrinogen concentration and Factors V, VII, and VIII are decreased. Prothrombin time and thromboplastin time are increased.

Platelet aggregation: High levels of plasma diatrizoates inhibit platelet aggregation.

Serum calcium: Diatrizoate salts may decrease serum calcium levels. However, this depletion of serum calcium may also be the result of the addition of chelating agents (edetate disodium) in the preparation of certain contrast media.

Red cell counts: Transitory decreases in red cell counts. Technetium-99m—RBC labeling interference.

Leukocyte counts: Decrease.

Urea nitrogen (BUN): Transitory increase (see CLINICAL PHARMACOLOGY).

Serum creatinine: Transitory increase.

Urine Tests

Contrast media which are excreted in the urine may interfere with some laboratory determinations, eg, proteinuria, specific gravity, osmolality, or bacterial cultures.

Thyroid Function Tests

Protein-bound iodine (PBI) and total serum organic iodine: Transient increase of both tests following urography have been noticed. The results of PBI and radioactive iodine uptake studies which depend on iodine estimations will not accurately reflect thyroid function for up to 16 days following administration of iodinated urographic media. However, thyroid function tests not depending on iodine estimations, eg, T3 resin uptake or free thyroxine assays, are not affected.

Carcinogenesis, Mutagenesis, Impairment of Fertility

Long-term studies in animals have not been performed in order to evaluate carcinogenic potential, mutagenesis, or whether HYPAQUE-76 can affect fertility in males or females.

Pregnancy Category C

Animal reproduction studies have not been conducted with HYPAQUE-76. It is also not known whether HYPAQUE-76 can cause fetal harm when administered to a pregnant woman or can affect reproduction capacity. HYPAQUE-76 should be given to a pregnant woman only if clearly needed.

Labor and Delivery

It is not known whether use of these contrast agents during labor or delivery has immediate or delayed adverse effects on the fetus, prolongs the duration of labor or increases the likelihood that forceps delivery or other obstetrical intervention or resuscitation of the newborn will be necessary.

Nursing Mothers

Diatrizoate salts are excreted unchanged in human milk. Because of the potential adverse reactions, although it has not been established that serious adverse reactions occur in nursing infants, caution should be exercised when these contrast media are administered to a nursing woman.

Pediatric Use

Infants and small children should not have any fluid restriction prior to excretory urography or any other procedures (see PRECAUTIONS—General). Guidelines for pediatric dosages are presented in DOSAGE AND ADMINISTRATION—General.

ADVERSE REACTIONS—General

Approximately 95 percent of adverse reactions accompanying the intravascular use of diatrizoate salts are of mild to moderate severity. However, life-threatening reactions and fatalities, mostly of cardiovascular origin, have occurred.

Adverse reactions to injectable contrast media fall into two categories: chemotoxic reactions and idiosyncratic reactions.

Chemotoxic reactions result from the physicochemical properties of the contrast media, the dose, and the speed of injection. All hemodynamic disturbances and injuries to organs or vessels perfused by the contrast medium are included in this category.

Idiosyncratic reactions include all other reactions. They occur more frequently in patients 20 to 40 years old. Idiosyncratic reactions may or may not be dependent on the amount of dose injected, the speed of injection, the mode of injection, and the radiographic procedure. Idiosyncratic reactions are subdivided into minor, intermediate, and severe. The minor reactions are self-limited and of short duration; the severe reactions are life-threatening and treatment is urgent and mandatory.

The reported incidence of adverse reactions to contrast media in patients with a history of allergy are twice that of the general population. Patients with a history of previous reactions to a contrast medium are three times more susceptible than other patients. However, sensitivity to contrast media does not appear to increase with repeated examinations.

Most adverse reactions to injectable contrast media appear within one to three minutes after the start of injection, but delayed reactions may occur.

Adverse reactions are grouped by organ system and listed below by decreasing order of occurrence and with an approximate incidence of occurrence. Significantly more severe reactions are listed before the other reactions regardless of frequency.

Greater Than 1 in 100 Patients

Body as a Whole: Reported incidences of death range from 6.6 per 1 million (0.00066 percent) to 1 in 10,000 patients (0.01 percent). Most deaths occur during injection or 5 to 10 minutes later, the main feature being cardiac arrest with cardiovascular disease as the main aggravating factor.

Isolated reports of hypotensive collapse and shock following urography are found in the literature. The incidence of shock is estimated to occur in 1 out of 20,000 (0.005 percent) patients.

Cardiovascular System: The most frequent adverse reaction to diatrizoate salts is vasodilation (feeling of warmth). The estimated incidence is 49 percent.

Digestive System: Nausea 6 percent, vomiting 3 percent.

Nervous System: Paresthesia 6 percent, dizziness 5 percent.

Respiratory System: Rhinitis 1 percent, increased cough 2 percent.

Skin and Appendages: Urticaria 1 percent.

Pain at the injection site is estimated to occur in about 12 percent of the patients undergoing urography. Pain is usually due to extravasation.

Painful hot erythematous swelling above the venipuncture site was estimated to occur in more than one percent of the patients undergoing phlebography.

Special Senses: Perversion of taste 11 percent.

Urogenital System: Osmotic nephrosis of the proximal tubular cells is estimated to occur in 23 percent of patients following excretory urography.

Less Than 1 in 100 Patients

Other infrequently reported reactions without accompanying incidence rates are listed below, grouped by organ system.

Body as a Whole: Malaria relapse, uremia, high creatinine and BUN (see PRECAUTIONS—General, Drug/Laboratory Test Interactions), thrombocytopenia, leukopenia, and anemia.

Cardiovascular System: Cerebral hematomas, hemodynamic disturbances, sinus bradycardia, transient electrocardiographic abnormalities, ventricular fibrillation, petechiae, chest pain, and cardiac arrest.

Digestive System: Severe unilateral or bilateral swelling of the parotid and submaxillary glands.

Nervous System: Convulsions, paralysis, and coma. (See PRECAUTIONS—General.)

Respiratory System: Asthma, dyspnea, laryngeal edema, pulmonary edema, and bronchospasm.

Skin and Appendages: Extravasation necrosis, urticaria with or without pruritus, mucocutaneous edema, and angioneurotic edema.

Special Senses: Bilateral ocular irritation, lacrimation, itching, conjunctival chemosis, infection, and conjunctivitis.

Urogenital: Renal failure, pain.

OVERDOSAGE

At dosage levels of diatrizoate sodium above a level containing 45 g of iodine, the incidence of unpleasant side effects increases. At total dosage equivalent to 80 gI or 90 gI administered over a short period of time (e.g., 30 minutes), clinical signs of systemic intolerance appear (mostly related to hyperosmolar effects) and are manifest as tremors, irritability, and tachycardia. Above these maximal tolerated dosage levels in otherwise healthy adults, an increasing incidence and severity of dyspnea and pulmonary edema should be expected.

Four cases of overdosage in infants, during urography, are reported. Three of the infants died within 19 hours of the injection. The overdose ranged from slightly above the recommended pediatric dosage to a dose exceeding 19 g/kg. The symptoms of overdosage appeared between 10 minutes to several hours after injection of the contrast medium. Adverse effects were life-threatening, affecting mainly the pulmonary and cardiovascular systems. The symptoms included: cyanosis, bradycardia, acidosis, pulmonary hemorrhage, convulsions, coma, and cardiac arrest. All infants showed a poor visualization of the kidneys and a diffuse opacification of all the tissues and vasculature. Autopsy findings showed acute pulmonary damage and/or edema of subcutaneous tissues. Treatment of an overdose of injectable radiopaque contrast media is directed toward the support of all vital functions, and prompt institution of symptomatic therapy.

The acute intravenous LD50 of diatrizoate salts in mice is equivalent in iodine content of 5.3 gI/kg to 8.0 gI/kg and seems to be directly proportioned to the rate of injection.

Diatrizoate salts are dialyzable.

DOSAGE AND ADMINISTRATION—General

Preparation of the patient will vary with preference of the radiologist and the type of radiological procedure performed. Specific radiographic procedures used will depend on the state of the patient and the diagnostic indications. Individual dose should be tailored according to age, body size, and indication for examination. (See INDIVIDUAL INDICATIONS AND USAGE section for specific Dosage and Administration.)

Solutions of radiopaque diagnostic agents for intravascular use should be at body temperature when injected and may need to be warmed before use. In the event that crystallization occurs, the solution may be clarified by placing the vial in a water bath at 40°C to 50°C and shaking it gently for two to three minutes or until the solids redissolve. If the particles still persist, do not use this vial but discard it. The solution may be autoclaved once.

The solution should be stored at room temperature and protected from strong light and any unused portion remaining in the container should be discarded.

Dilution and withdrawal of the contrast agents should be accomplished under aseptic conditions with sterile syringes.

Parenteral drug products should be inspected visually for particulate matter and discoloration prior to administration. Avoid contaminating catheters, syringes, needles, and contrast media with glove powder or cotton fibers.

Pediatric Dosage

Pediatric doses of injectable radiopaque diagnostic agents are generally determined on a weight basis and should be calculated for each patient individually. (See INDIVIDUAL INDICATIONS AND USAGE section.)

Drug Incompatibilities

Diatrizoate salts are incompatible in vitro with some antihistamines and many other drugs. It is believed that one of the chief causes of in vitro incompatibility is an alteration of pH. Turbidity of solutions of intravascular contrast medium occurs between pH 2.5 and 4.1. Another cause is chemical interaction; therefore, other pharmaceuticals should not be mixed with contrast agents in the same syringe.

INDIVIDUAL INDICATIONS AND USAGE

THE FOLLOWING SECTIONS FOR INDIVIDUAL INDICATIONS AND USAGE CONTAIN CONTRAINDICATIONS, WARNINGS, PRECAUTIONS, ADVERSE REACTIONS, AND DOSAGE AND ADMINISTRATION SECTIONS RELATED TO THE SPECIFIC PROCEDURES. HOWEVER, IT SHOULD BE UNDERSTOOD THAT THE INFORMATION IN THE GENERAL SECTIONS IS ALSO LIKELY TO APPLY TO ALL OF THESE SPECIFIC USES.

Hydration: With the possible exception of urography, patients should be fully hydrated prior to the following procedures.

EXCRETORY UROGRAPHY

Diatrizoate salts are used in small, medium, and large dose urography. Visualization of the urinary tract can be achieved by either direct intravenous bolus injection, intravenous drip infusion, or incidentally following intra-arterial procedures. Visualization of the urinary tract is delayed in infants less than 1 month old, and in patients with urinary tract obstruction (see CLINICAL PHARMACOLOGY).

Nephrotomography and "Adequate" or High Dose Urography

HYPAQUE-76 solution may be used for excretory urography in selected patients. It may be used when prior urography has failed to provide diagnostic contrast and for preliminary excretory tract study to detect obstruction in azotemic patients or to avoid retrograde instrumentation. It may also be used as a high dosage medium to intensify and prolong the nephrographic effect when the prime purpose is examination of the renal parenchyma, especially with tomography. When combined with the urea "washout" technique, HYPAQUE-76 provides the necessary increased pyelographic contrast and diuresis required for screening or special examination of patients with suspected renal hypertension.

Contraindication

Urography is contraindicated in patients with anuria.

Precautions

Although azotemia is not considered a contraindication, care is required in patients with advanced renal failure. The usual preparatory dehydration should be omitted, and urinary output should be observed for one to two days in these patients. Adequate visualization may be difficult or impossible to attain in patients with severely impaired renal and/or hepatic function. Use with extreme caution in patients with concomitant hepatorenal disease.

When HYPAQUE-76 is used with a urea "washout" procedure, the patient should also be observed for a few hours to detect signs of undue dehydration caused by increased diuresis induced by both the medium and the urea. Ingestion of water may be required for rehydration.

In myelomatosis, urography should only be performed with caution. If a weak protein-binding agent such as a diatrizoate is used for the procedure, it is essential to omit preparatory dehydration, administer fluids, and attempt to alkalinize the urine.

Preparatory Dehydration: Preparatory dehydration is dangerous in infants, young children, the elderly, and azotemic patients (especially those with polyuria, oliguria, diabetes, advanced vascular disease, or preexisting dehydration). The undesirable dehydration in these patients may be accentuated by the osmotic diuretic action of the medium.

Dehydration may improve image quality in patients with adequate renal function particularly if a low dose is used. Dehydration, however, will not improve contrast quality in patients with substantial renal insufficiencies and will increase risk of contrast induced renal damage. Dehydration in these patients is therefore contraindicated.

Adverse Reactions

Side effects following this relatively high dose urography are usually mild and transitory and do not appear to occur more frequently or severely than those induced by "standard dose" urography. Nausea, facial flushing, and emesis are not uncommon reactions. (See also ADVERSE REACTIONS—General.)

Dosage and Administration

The usual intravenous dose for adults is 20 mL, with a range of 20 mL to 40 mL. Children require less in proportion to weight: Under 6 months of age—4 mL; 6 to 12 months—6 mL; 1 to 2 years—8 mL; 2 to 5 years—10 mL; 5 to 7 years—12 mL; 8 to 10 years—14 mL; 11 to 15 years—16 mL.

ANGIOGRAPHY—General

Diatrizoate salts are used for radiographic studies throughout the cardiovascular system.

Intravascular radiopaque diagnostic agents of high concentration are not recommended for cerebral or spinal angiography (see CONTRAINDICATIONS—General), and contrast agents with the lowest compatible viscosity and higher concentration of iodine (310 mg/mL to 480 mg/mL of bound iodine) must be used for angiocardiography. Contrast media approaching serum ionic content and osmolality have less potential for deleterious effects on the myocardium (see PRECAUTIONS—General, Drug Interactions).

Addition of chelating agents may contribute to toxicity in coronary angiography, and the sodium content of angiographic agents used in coronary arteriography is of crucial importance.

AORTOGRAPHY

HYPAQUE-76 solution may be injected by commonly accepted techniques, such as translumbar, retrograde catheter, retrograde pressure injection (by cannula) or antegrade (brachial) catheter, for examination of the aorta and its major branches.

Warnings

During aortography by the translumbar technique, extreme care is advised to avoid inadvertent intrathecal injection since the injection of even small amounts (5 mL to 7 mL) of the contrast medium may cause convulsions, permanent sequelae, or fatality. Should the accident occur, the patient should be placed upright to confine the hyperbaric solution to a low level, anesthesia may be required to control convulsions, and if there is evidence of a large dose having been administered, a careful cerebrospinal fluid exchange-washout should be considered.

Pheochromocytoma: Administration of angiographic media to patients known or suspected to have pheochromocytoma can cause dangerous changes in blood pressure. A minimum dose should be injected. The blood pressure should be carefully monitored and measures for controlling major fluctuations should be available.

Precautions

The presence of a vigorous pulsatile flow should be established before using a catheter or pressure injection technique. A small "pilot" dose (about 2 mL) should be administered to locate the exact site of needle or catheter tip to help prevent injection of the main dose into a branch of the aorta or intramurally. In the translumbar technique, severe pain during injection may indicate intramural placement and abdominal or back pain afterwards may indicate hemorrhage from the injection site. Following catheter procedures, gentle pressure hemostasis for 5 to 10 minutes is advised, followed by observation for 30 to 60 minutes and immobilization of the limb for several hours to prevent hemorrhage from the site of arterial puncture.

Under conditions of slowed aortic circulation there is an increased likelihood of aortography causing muscle spasm. Occasional serious neurologic complications, including paraplegia, have also been reported in patients with aortic-iliac or even femoral artery bed obstruction, abdominal compression, hypotension, hypertension, spinal anesthesia, injection of vasopressors to increase contrast, and low injection sites (L2-3). In these patients the concentration, dose, and number of repeat injections of the medium should be maintained at a minimum with appropriate intervals between injections. The position of the patient and catheter tip should be carefully evaluated.

Adverse Reactions

The only adverse reaction expected is a mild burning or painful sensation on injection. Unusual reactions can occur, as in angiocardiography. An abrupt hypertensive episode can occur following entry of the medium into the renal artery in patients with pheochromocytoma. Mesenteric necrosis, acute pancreatitis, renal shutdown (usually transitory), and neurologic complications have been reported following inadvertent injection of a large part of the aortic dose into a branch of the aorta. Entry of the large aortic dose into the renal artery can cause, even in the absence of symptoms, albuminuria, cylindruria, hematuria, and an elevated BUN. Rapid and complete return of function usually follows.

Additional procedural reactions include injury to the aorta and neighboring organs, pleural puncture, renal damage including infarction and acute tubular necrosis with oliguria and anuria, accidental selective filling of the right renal artery during the translumbar procedure in the presence of preexistent renal disease, and retroperitoneal hemorrhage from the translumbar approach.

Dosage and Administration

Adult: The usual adult dose as a single injection is 15 mL to 40 mL, repeated if indicated, to a total of 160 mL.

Pediatric: The usual single pediatric dose ranges from 0.3 mL/kg to 0.9 mL/kg. The total dose should not exceed 1 mL/kg.

ANGIOCARDIOGRAPHY

Pharmacology-Hemodynamic Changes

Due to its physical characteristics (chiefly tonicity and viscosity) and the volume administered, HYPAQUE-76 may cause a number of transitory hemodynamic changes. When the medium is ejected from the left ventricle or introduced at the root of the ascending aorta, a brief (three seconds) hypertensive response is usually induced, followed immediately by a decrease in aortic and peripheral blood pressures below normal levels, lasting for at least two minutes. This hypotensive phase may be followed by a 15- to 20-minute period of fluctuating blood pressure.

Clinical doses (up to 1 mL per kg) injected into the vena cava or right heart outflow tract usually cause an irregular rise in right ventricular blood pressure, a slight increase in pulmonary artery blood pressure, and delayed signs of peripheral hypotension.

Other changes reported clinically include an increase in cardiac output and atrial pressure, a decrease in myocardial contractile force, and at the peak of postinjection hypotension, a marked rise in aortic and carotid blood flow, and elevation of central venous pressure. At dosage levels used in angiocardiography, the hematocrit and hemoglobin level may fall about 10 to 15 percent and serum osmolality may rise 10 to 12 percent. Blood carbon dioxide, pH, and BUN levels may fall. These changes commence immediately after injection, reach a maximum in two to five minutes, and return to normal values in 10 to 15 minutes. However, after the initial rise, plasma volume may decrease and continue to fall below control levels, even beyond 30 minutes, probably due to diuresis. If repeat injections are made in rapid succession these changes are likely to be more pronounced. (See also Dosage and Administration.) HYPAQUE-76 is not metabolized. It is eliminated unchanged, rapidly and completely in the urine by glomerular filtration.

Precautions

During administration of large doses of HYPAQUE-76 continuous monitoring of vital signs is desirable. Caution is advised in the administration of large doses to patients with incipient heart failure because of the possibility of aggravation of the preexisting condition. Hypotension should be corrected promptly since it may induce serious arrhythmias.

Because of the hemodynamic changes which may occur on injection into the right heart outflow tract, special care, especially regarding dosage, should be observed in patients with right ventricular failure, pulmonary hypertension, or obliterated pulmonary vascular beds.

Precautions in Infants

Apnea, bradycardia and other arrhythmias, cerebral effects (lethargy and depression), and a tendency to acidosis are more likely to occur in cyanotic infants. It is desirable that vital signs be monitored on an intensive care basis afterwards to detect delayed adverse effects (arrhythmia, electrolyte and hemodynamic disturbances). Infants are more likely than adults to respond with convulsions, particularly after repeated injections. Unlike in the adult, the amount of the total dosage in young infants is of particular importance. (See Dosage and Administration.)

Adverse Reactions

See ADVERSE REACTIONS—General.

Dosage and Administration

The individual dose is determined by the size of the structure to be visualized, the anticipated degree of hemodilution, and valvular competence. Weight is a minor consideration in adults. The size of each individual dose is a more important consideration than the total dosage used. When large individual doses are administered, as for contrast in the cardiac chambers and thoracic aorta, it has been suggested that 20 minutes be permitted to elapse between each injection to allow for subsidence of hemodynamic disturbances.

Ventriculography

Adult: The usual adult dose in a single injection is 45 mL, with a range of 40 mL to 50 mL. This may be repeated as necessary. However, when combined with selective coronary arteriography, the total dose should not exceed 225 mL.

Pediatric: The usual single pediatric dose is 0.2 mL/kg to 0.3 mL/kg. The total dose should not exceed 50 mL.

Pulmonary Angiography or Arch Study Used Alone

Adult: The usual single adult dose is 30 mL, with a range of 10 mL to 56 mL.

Pediatric: The pediatric dose ranges from 0.3 mL/kg to 0.9 mL/kg. The total dose should not exceed 1 mL/kg.

Combined Angiocardiographic Procedures

Multiple Procedures

With continuing advances in radiologic techniques and the development of more sophisticated equipment as well as more versatile and reliable radiopaque media, it is possible to examine multiple vascular systems and target organs during a single radiographic examination of the patient.

Multiple procedures of selective angiography require multiple injections of the contrast medium into several specific target organs and result in a greater dosage. Large doses of HYPAQUE-76 were well tolerated in multiple injections and multiple procedures of angiography.

See general sections for Contraindications, Warnings, Precautions, Adverse Reactions, and Dosage and Administration recommendations as well as those sections pertinent to the specific procedures.

Adult: The maximum total dose for multiple procedures in adult use should not exceed 225 mL.

Pediatric: When multiple procedures are required in pediatric use, the total dose administered should be maintained below 4 mL/kg, or especially in young infants below 3 mL/kg.

Selective Coronary Arteriography

Adult: The usual single adult dose for right or left coronary arteriography is 8 mL (range 4 mL to 10 mL) repeated as required up to a total dose of 120 mL for coronary arteriography alone.

PERIPHERAL ANGIOGRAPHY

The use of HYPAQUE-76 is sometimes preferred over less concentrated media in selected cases for femoral and brachio-axillary arteriography in adults.

Precautions

Pulsation should be present in the artery to be injected. In thromboangiitis obliterans, or ascending infection associated with severe ischemia, angiography should be performed with extreme caution, if at all.

Adverse Reactions

Pain or a burning sensation with some spasm may occur, and is more marked in patients with arterial insufficiency. Therefore, the procedure is more satisfactorily performed under general or, for the lower extremity, spinal anesthesia.

Technical complications have included hemorrhage from the puncture site, and brachial plexus palsy following axillary artery injections.

Arterial thrombosis, displacement of arterial plaques, and ipsilateral venous thrombosis are very rare complications.

Dosage and Administration

Arteriography (aorto-iliac runoff and peripheral)

Adult: The single adult dose for femoral arteriography varies from 20 mL to 40 mL, depending on the site of placement, i.e., aorta-iliac runoff, iliofemoral, femoral. For the upper limb, 20 mL to 40 mL is usually sufficient. These doses may be repeated up to three times.

VENOGRAPHY

Dosage and Administration

Central Venography

Adult: For central venography (inferior or superior vena cava), the total adult dose is 40 mL to 50 mL, repeated up to two times.

Renal Venography

Adult: The usual single adult dose is 20 mL to 40 mL.

Peripheral Venography

Adult: The usual single adult dose is 40 mL with a range of 40 mL to 60 mL.

SELECTIVE RENAL ARTERIOGRAPHY

Dosage and Administration

Adult: The usual single adult dose is 8 mL, repeated up to three times. The dose ranges from 5 mL to 10 mL.

SELECTIVE VISCERAL ARTERIOGRAPHY

Dosage and Administration

Celiac Axis: The usual adult dose ranges from 30 mL to 40 mL with subselective arteriography of its branches, e.g., hepatic, usual dose of 25 mL with a range of 15 mL to 30 mL; mesenteric, usual dose of 30 mL with a range of 20 mL to 40 mL; splenic, usual dose of 20 mL with a range of 20 mL to 50 mL.

Superior Mesenteric: The usual single adult dose is 30 mL with a range of 20 mL to 40 mL. The maximum total dose should not exceed 175 mL.

INTRAVENOUS DIGITAL ARTERIOGRAPHY

Arteriograms of diagnostic quality can be obtained following the intravenous administration of HYPAQUE-76 employing digital subtraction and computer imaging enhancement equipment. The intravenous route of administration using these techniques has the advantage of being less invasive than the corresponding selective catheter placement of the medium. The dose is administered into a peripheral vein usually by mechanical injection although sometimes by rapid manual injection. The technique has been used most frequently to visualize the ventricles, the aorta and most of its larger branches including carotid, cerebral, vertebral, renal, celiac, mesenterics, and the major peripheral vessels of the limbs.

Precautions

Since the dose is usually administered mechanically under high pressure, rupture of smaller peripheral veins has occurred. It has been suggested that this can be avoided by using an intravenous catheter threaded proximally beyond larger tributaries or in the case of the antecubital vein, into the superior vena cava. Sometimes the femoral vein is used.

Dosage and Administration

The usual dose of HYPAQUE-76 per injection by the intravenous digital technique is 30 mL to 60 mL with a range of 0.5 mL/kg to 1 mL/kg administered as a bolus 7.5 mL/second to 30 mL/second using a pressure injector. The dose and rate of injection will depend primarily on the type of equipment and technique used, with first exposures made on calculated circulation time.

CONTRAST ENHANCEMENT OF COMPUTED TOMOGRAPHIC HEAD IMAGING

Injectable radiopaque contrast media may be used to refine diagnostic precision in areas of the brain which may not otherwise have been satisfactorily visualized.

Tumors: Radiopaque diagnostic agents may be useful to investigate the presence and extent of certain malignancies such as: gliomas including malignant gliomas, glioblastomas, astrocytomas, oligodendrogliomas and gangliomas, ependymomas, medulloblastomas, meningiomas, neuromas, pinealomas, pituitary adenomas, craniopharyngiomas, germinomas, and metastatic lesions. The usefulness of contrast enhancement for the investigation of the retrobulbar space and in cases of low grade or infiltrative glioma has not been demonstrated.

In calcified lesions, there is less likelihood of enhancement. Following therapy, tumors may show decreased or no enhancement.

Nonneoplastic Conditions of the Brain: The use of HYPAQUE-76 may be beneficial in the enhancement of images of lesions not due to neoplasms. Cerebral infarctions of recent onset may be better visualized with the contrast enhancement, while some infarctions are obscured if a contrast medium is used. The use of HYPAQUE-76 improved the contrast enhancement in approximately 60 percent of cerebral infarctions studied from one week to four weeks from the onset of symptoms.

Sites of active infection also will produce contrast enhancement following contrast medium administration.

Arteriovenous malformations and aneurysms will show contrast enhancement. In the case of these vascular lesions, the enhancement is probably dependent on the iodine content of the circulating blood pool.

Hematomas and intraparenchymal bleeders seldom demonstrate any contrast enhancement. However, in cases of intraparenchymal clot, for which there is no obvious clinical explanation, contrast medium administration may be helpful in ruling out the possibility of associated arteriovenous malformation.

The opacification of the inferior vermis following contrast medium administration has resulted in false-positive diagnoses in a number of normal studies.

Dosage and Administration

The suggested dose is 50 mL to 125 mL by intravenous administration; scanning may be performed immediately after completion of administration. Doses for children should be proportionately less, depending on age and weight.

CONTRAST ENHANCEMENT OF COMPUTED TOMOGRAPHIC BODY IMAGING

HYPAQUE-76, brand of diatrizoate meglumine and diatrizoate sodium injection, may be used for enhancement of computed tomographic scans performed for detection and evaluation of lesions in the liver, pancreas, kidneys, aorta, mediastinum, abdominal cavity, pelvis, and retroperitoneal space.

Enhancement of computed tomography with HYPAQUE-76 may be of benefit in establishing diagnoses of certain lesions in these sites with greater assurance than is possible with CT alone, and in supplying additional features of the lesions (e.g., hepatic abscess delineation prior to percutaneous drainage). In other cases, the contrast agent may allow visualization of lesions not seen with CT alone (e.g., tumor extension), or may help to define suspicious lesions seen with unenhanced CT (e.g., pancreatic cyst).

Contrast enhancement appears to be greatest within 60 to 90 seconds after bolus administration of the contrast agent. Therefore, utilization of a continuous scanning technique (dynamic CT scanning) may improve enhancement and diagnostic assessment of tumor and other lesions such as an abscess, occasionally revealing unsuspected or more extensive disease. For example, a cyst may be distinguished from a vascularized solid lesion when precontrast and enhanced scans are compared; the nonperfused mass shows unchanged x-ray absorption (CT number). A vascularized lesion is characterized by an increase in CT number in the few minutes after a bolus of intravascular contrast agent; it may be malignant, benign or normal tissue, but would probably not be a cyst, hematoma, or other nonvascular lesion.

Because unenhanced scanning may provide adequate diagnostic information in the individual patient, the decision to employ contrast enhancement, which may be associated with risk and increased radiation exposure, should be based upon a careful evaluation of clinical, other radiological and unenhanced CT findings.

Dosage and Administration

The suggested dose is 50 mL to 125 mL by rapid intravenous bolus administration; scanning may be performed immediately after completion of administration. Doses for children should be proportionately less, depending on age and weight.

HOW SUPPLIED

Vials of 50 mL, rubber stoppered, box of 25 (NDC 0407-0776-04)

Calibrated bottles of 200 mL, rubber stoppered, with hangers, box of 10 (NDC 0407-0778-02)

Distributed by Amersham Health Inc.
Princeton, NJ 08540

Printed In USA

HNC-9D